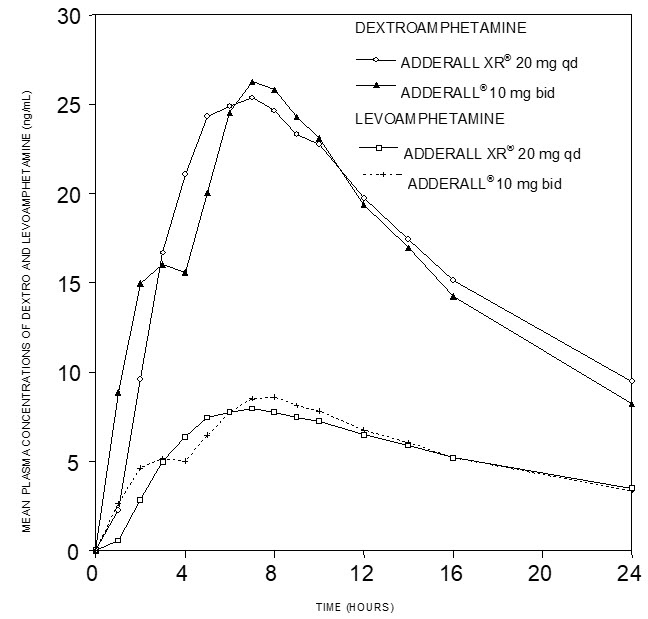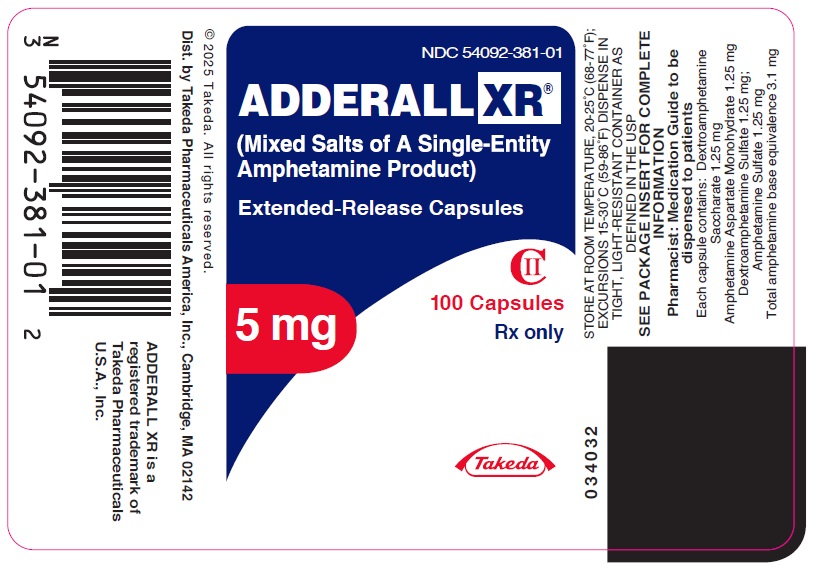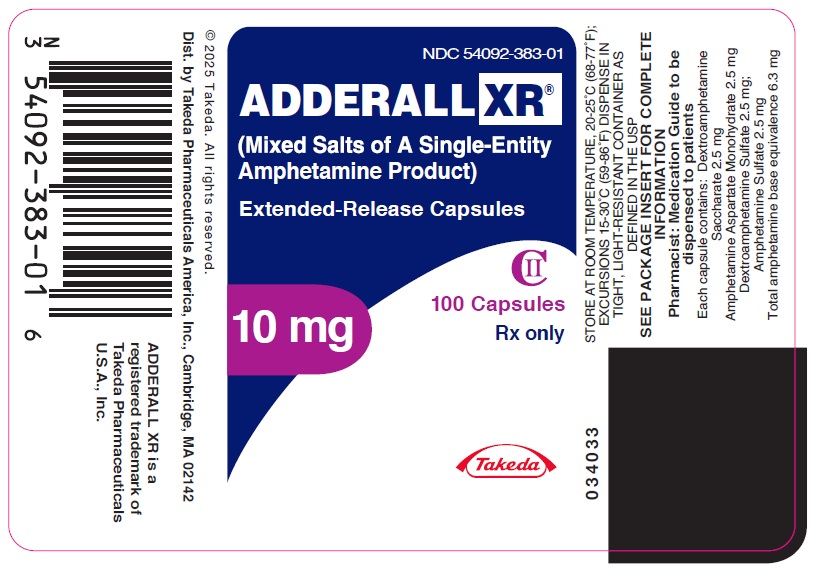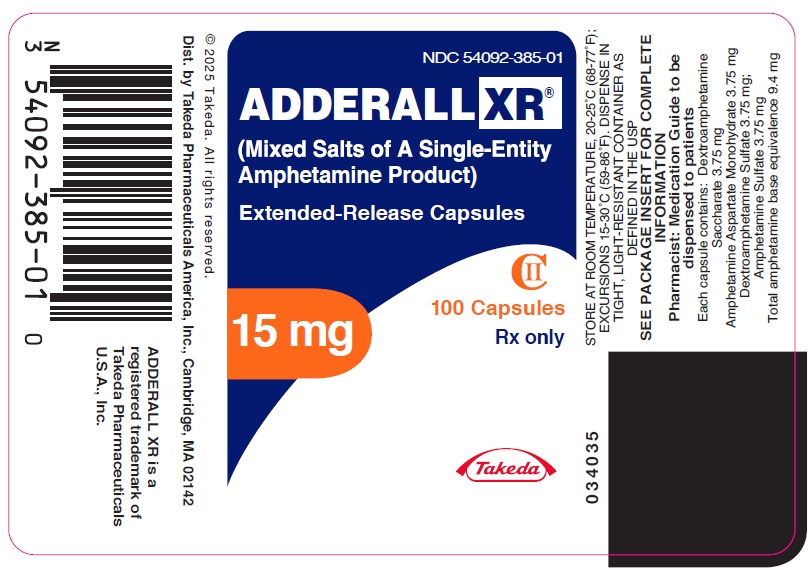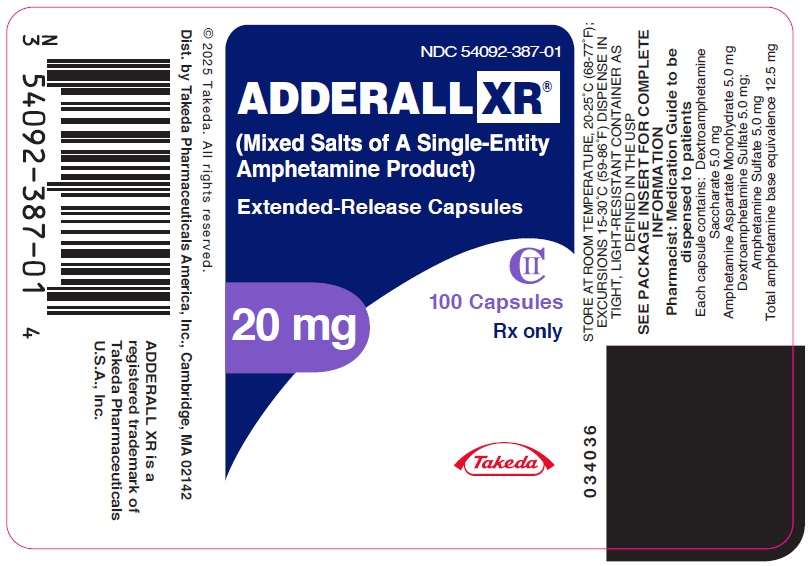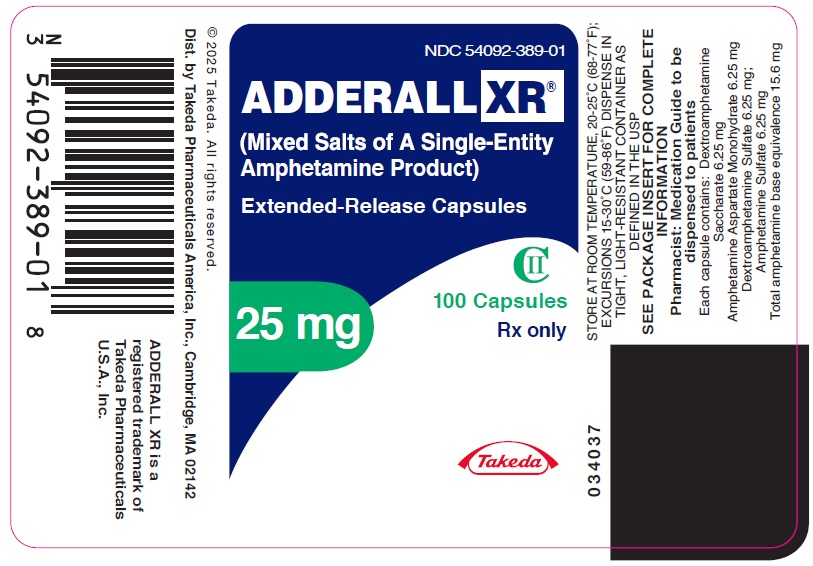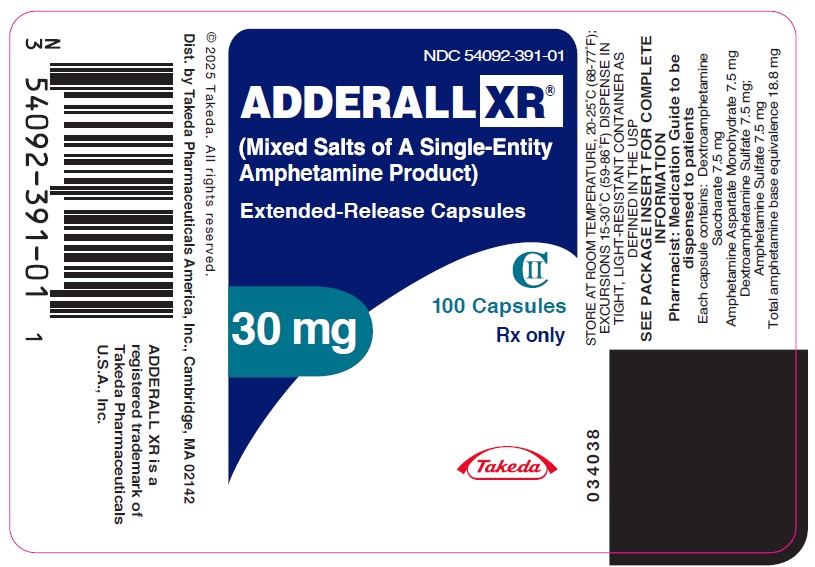 DRUG LABEL: Adderall
NDC: 54092-381 | Form: CAPSULE, EXTENDED RELEASE
Manufacturer: Takeda Pharmaceuticals America, Inc.
Category: prescription | Type: HUMAN PRESCRIPTION DRUG LABEL
Date: 20250923
DEA Schedule: CII

ACTIVE INGREDIENTS: DEXTROAMPHETAMINE SULFATE 1.25 mg/1 1; DEXTROAMPHETAMINE SACCHARATE 1.25 mg/1 1; AMPHETAMINE ASPARTATE MONOHYDRATE 1.25 mg/1 1; AMPHETAMINE SULFATE 1.25 mg/1 1
INACTIVE INGREDIENTS: GELATIN, UNSPECIFIED; HYPROMELLOSE, UNSPECIFIED; METHACRYLIC ACID - METHYL METHACRYLATE COPOLYMER (1:1); SUCROSE; TALC; TRIETHYL CITRATE; FD&C BLUE NO. 2; TITANIUM DIOXIDE

HIGHLIGHTS OF PRESCRIBING INFORMATION

These highlights do not include all the information needed to use ADDERALL XR safely and effectively. See full prescribing information for ADDERALL XR.
ADDERALL XR® (mixed salts of a single-entity amphetamine product) extended-release capsules, for oral use, CII
Initial U.S. Approval: 2001

WARNING: ABUSE, MISUSE, and ADDICTION

See full prescribing information for complete boxed warning.

ADDERALL XR has a high potential for abuse and misuse, which can lead to the development of a substance use disorder, including addiction. Misuse and abuse of CNS stimulants, including ADDERALL XR, can result in overdose and death (5.1, 9.2, 10):

- Before prescribing ADDERALL XR, assess each patient’s risk for abuse, misuse, and addiction.
- Educate patients and their families about these risks, proper storage of the drug, and proper disposal of any unused drug.
- Throughout treatment, reassess each patient’s risk and frequently monitor for signs and symptoms of abuse, misuse, and addiction.

RECENT MAJOR CHANGES

Indications and Usage (1) | 09/2025
Warnings and Precautions (5.5) | 09/2025

1 INDICATIONS AND USAGE

ADDERALL XR, a CNS stimulant, is indicated for the treatment of attention deficit hyperactivity disorder (ADHD) in adults and pediatric patients 6 years and older. (1)

Limitations of Use
The use of ADDERALL XR is not recommended in pediatric patients younger than 6 years of age because they had higher plasma exposure and a higher incidence of adverse reactions (e.g., weight loss) than patients 6 years and older at the same dosage. (5.5, 8.4)

2 DOSAGE AND ADMINISTRATION

- Pediatric patients (ages 6 to 17): 10 mg once daily in the morning. Maximum dose for children 6 to 12 years of age is 30 mg once daily. (2.2, 2.3, 2.4)
- Adults: 20 mg once daily in the morning. (2.5)
- Pediatric patients (ages 6 to 17) with severe renal impairment: 5 mg once daily in the morning. Maximum dose for children 6 to 12 years of age with severe renal impairment is 20 mg once daily. (2.6, 8.6)
- Adults with severe renal impairment: 15 mg once daily in the morning. (2.6, 8.6)
- Patients with end stage renal disease (ESRD): Not recommended. (2.6, 8.6)

3 DOSAGE FORMS AND STRENGTHS

Extended-release capsules: 5 mg, 10 mg, 15 mg, 20 mg, 25 mg, 30 mg (3)

4 CONTRAINDICATIONS

- Known hypersensitivity or idiosyncrasy to amphetamine. (4)
- During or within 14 days following the administration of monoamine oxidase inhibitors (MAOI). (4, 7.1)

5 WARNINGS AND PRECAUTIONS

- Risks to Patients with Serious Cardiac Disease: Avoid use in patients with known structural cardiac abnormalities, cardiomyopathy, serious cardiac arrhythmias, coronary artery disease, or other serious cardiac disease. (5.2)
- Increased Blood Pressure and Heart Rate: Monitor blood pressure and pulse at appropriate intervals. (5.3)
- Psychiatric Adverse Reactions: Prior to initiating ADDERALL XR, screen patients for risk factors for developing a manic episode. If new psychotic or manic symptoms occur, consider discontinuing ADDERALL XR. (5.4)
- Long-Term Suppression of Growth in Pediatric Patients: Closely monitor growth (height and weight) in pediatric patients. Pediatric patients not growing or gaining height or weight as expected may need to have their treatment interrupted. (5.5)
- Seizures: May lower the convulsive threshold. Discontinue in the presence of seizures. (5.6)
- Peripheral Vasculopathy, including Raynaud’s Phenomenon: Careful observation for digital changes is necessary during ADDERALL XR treatment. Further clinical evaluation (e.g., rheumatology referral) may be appropriate for patients who develop signs or symptoms of peripheral vasculopathy. (5.7)
- Serotonin Syndrome: Increased risk when coadministered with serotonergic agents (e.g., SSRIs, SNRIs, triptans), but also during overdosage situations. If it occurs, discontinue ADDERALL XR and initiate supportive treatment. (4, 5.8, 10)
- Motor and Verbal Tics, and Worsening of Tourette’s Syndrome: Before initiating ADDERALL XR, assess the family history and clinically evaluate patients for tics or Tourette’s syndrome. Regularly monitor patients for the emergence or worsening of tics or Tourette’s syndrome. Discontinue treatment if clinically appropriate. (5.9)

6 ADVERSE REACTIONS

- Pediatric patients ages 6 to 12: Most common adverse reactions (≥5% and with a higher incidence than on placebo) were loss of appetite, insomnia, abdominal pain, emotional lability, vomiting, nervousness, nausea, and fever. (6.1)
- Pediatric patients ages 13 to 17: Most common adverse reactions (≥5% and with a higher incidence than on placebo) were loss of appetite, insomnia, abdominal pain, weight loss, and nervousness. (6.1)
- Adults: Most common adverse reactions ≥5% and with a higher incidence than on placebo were dry mouth, loss of appetite, insomnia, headache, weight loss, nausea, anxiety, agitation, dizziness, tachycardia, diarrhea, asthenia, and urinary tract infections. (6.1)

To report SUSPECTED ADVERSE REACTIONS, contact Takeda Pharmaceuticals U.S.A., Inc. at 1-877-TAKEDA-7 (1-877-825-3327) or FDA at 1-800-FDA-1088 or www.fda.gov/medwatch.

7 DRUG INTERACTIONS

- Alkalinizing agents (GI antacids and urinary): These agents increase blood levels of amphetamine. (2.7, 7.1)
- Acidifying agents (GI and urinary): These agents reduce blood levels of amphetamine. (7.1)

8 USE IN SPECIFIC POPULATIONS

- Pregnancy: May cause fetal harm. (8.1)
- Lactation: Breastfeeding not recommended. (8.2)

FULL PRESCRIBING INFORMATION

WARNING: ABUSE, MISUSE, and ADDICTION

ADDERALL XR has a high potential for abuse and misuse, which can lead to the development of a substance use disorder, including addiction. Misuse and abuse of CNS stimulants, including ADDERALL XR, can result in overdose and death [see Overdosage (10)], and this risk is increased with higher doses or unapproved methods of administration, such as snorting or injection.

Before prescribing ADDERALL XR, assess each patient’s risk for abuse, misuse, and addiction. Educate patients and their families about these risks, proper storage of the drug, and proper disposal of any unused drug. Throughout ADDERALL XR treatment, reassess each patient’s risk of abuse, misuse, and addiction and frequently monitor for signs and symptoms of abuse, misuse, and addiction [see Warnings and Precautions (5.1), Drug Abuse and Dependence (9.2)].

1 INDICATIONS AND USAGE

1.1 Attention Deficit Hyperactivity Disorder

ADDERALL XR® is indicated for the treatment of attention deficit hyperactivity disorder (ADHD) in adults and pediatric patients 6 years and older.

Limitations of Use
The use of ADDERALL XR is not recommended in pediatric patients younger than 6 years of age because they had higher plasma exposure and a higher incidence of adverse reactions (e.g., weight loss) than patients 6 years and older at the same dosage [see Warnings and Precautions (5.5), Use in Specific Populations (8.4)].

2 DOSAGE AND ADMINISTRATION

2.1 Pretreatment Screening

Prior to treating patients with ADDERALL XR, assess:

- for the presence of cardiac disease (i.e., perform a careful history, family history of sudden death or ventricular arrhythmia, and physical exam) [see Warnings and Precautions (5.2)].
- the family history and clinically evaluate patients for motor or verbal tics or Tourette’s syndrome before initiating ADDERALL XR [see Warnings and Precautions (5.9)].

2.2 General Administration Information

Individualize the dosage according to the therapeutic needs and response of the patient. Administer ADDERALL XR at the lowest effective dosage.

Based on bioequivalence data, patients taking divided doses of immediate-release ADDERALL, (for example, twice daily), may be switched to ADDERALL XR at the same total daily dose taken once daily. Titrate at weekly intervals to appropriate efficacy and tolerability as indicated.

ADDERALL XR extended-release capsules may be taken whole, or the capsule may be opened and the entire contents sprinkled on applesauce. If the patient is using the sprinkle administration method, the sprinkled applesauce should be consumed immediately; it should not be stored. Patients should take the applesauce with sprinkled beads in its entirety without chewing. The dose of a single capsule should not be divided. The contents of the entire capsule should be taken, and patients should not take anything less than one capsule per day.

ADDERALL XR may be taken orally with or without food.

ADDERALL XR should be given upon awakening. Afternoon doses should be avoided because of the potential for insomnia.

2.3 Recommended Dosage in Pediatric Patients 6 to 12 Years

In pediatric patients 6 to 12 years of age with ADHD and are either starting treatment for the first time or switching from another medication, start with 10 mg once daily in the morning; daily dosage may be adjusted in increments of 5 mg or 10 mg at weekly intervals. When in the judgment of the clinician a lower initial dose is appropriate, patients may begin treatment with 5 mg once daily in the morning.

The maximum recommended dose for children 6 to 12 years of age is 30 mg/day; doses greater than 30 mg/day have not been studied in children. ADDERALL XR has not been studied in children under 6 years of age.

2.4 Recommended Dosage in Pediatric Patients 13 to 17 Years

The recommended starting dose for pediatric patients 13 to 17 years of age with ADHD and are either starting treatment for the first time or switching from another medication is 10 mg/day. The dose may be increased to 20 mg/day after one week if ADHD symptoms are not adequately controlled.

2.5 Recommended Dosage in Adults

In adults with ADHD who are either starting treatment for the first time or switching from another medication, the recommended dose is 20 mg/day.

2.6 Dosage in Patients with Renal Impairment

In adult patients with severe renal impairment (GFR 15 to <30 mL/min/1.73 m^2), the recommended dose is 15 mg once daily in the morning. In pediatric patients (6 to 17 years of age) with severe renal impairment, the recommended dose is 5 mg once daily. The maximum dose for children 6 to 12 years of age with severe renal impairment is 20 mg once daily. ADDERALL XR is not recommended in patients with end stage renal disease (ESRD) (GFR <15 mL/min/1.73 m^2) [see Use in Specific Populations (8.6), Clinical Pharmacology (12.3)].

2.7 Dosage Modification due to Drug Interactions

Agents that alter urinary pH can impact excretion and alter blood levels of amphetamines. Acidifying agents (e.g., ascorbic acid) decrease blood levels; adjust ADDERALL XR dosage based on clinical response [see Drug Interactions (7)].

3 DOSAGE FORMS AND STRENGTHS

ADDERALL XR 5 mg extended-release capsules: Clear/blue (imprinted ADDERALL XR 5 mg)

ADDERALL XR 10 mg extended-release capsules: Blue/blue (imprinted ADDERALL XR 10 mg)

ADDERALL XR 15 mg extended-release capsules: Blue/white (imprinted ADDERALL XR 15 mg)

ADDERALL XR 20 mg extended-release capsules: Orange/orange (imprinted ADDERALL XR 20 mg)

ADDERALL XR 25 mg extended-release capsules: Orange/white (imprinted ADDERALL XR 25 mg)

ADDERALL XR 30 mg extended-release capsules: Natural/orange (imprinted ADDERALL XR 30 mg)

4 CONTRAINDICATIONS

ADDERALL XR administration is contraindicated in patients:

- known to be hypersensitive to amphetamine, or other components of ADDERALL XR. Hypersensitivity reactions such as angioedema and anaphylactic reactions have been reported in patients treated with other amphetamine products [see Adverse Reactions (6.2)].
- taking monoamine oxidase inhibitors (MAOIs), or within 14 days of stopping MAOIs (including MAOIs such as linezolid or intravenous methylene blue), because of an increased risk of hypertensive crisis [see Warnings and Precautions (5.8), Drug Interactions (7.1)].

5 WARNINGS AND PRECAUTIONS

5.1 Abuse, Misuse, and Addiction

ADDERALL XR has a high potential for abuse and misuse. The use of ADDERALL XR exposes individuals to the risks of abuse and misuse, which can lead to the development of a substance use disorder, including addiction. ADDERALL XR can be diverted for non-medical use into illicit channels or distribution [see Drug Abuse and Dependence (9.2)]. Misuse and abuse of CNS stimulants, including ADDERALL XR, can result in overdose and death [see Overdosage (10)], and this risk is increased with higher doses or unapproved methods of administration, such as snorting or injection.

Before prescribing ADDERALL XR, assess each patient’s risk for abuse, misuse, and addiction. Educate patients and their families about these risks and proper disposal of any unused drug. Advise patients to store ADDERALL XR in a safe place, preferably locked, and instruct patients to not give ADDERALL XR to anyone else. Throughout ADDERALL XR treatment, reassess each patient’s risk of abuse, misuse, and addiction and frequently monitor for signs and symptoms of abuse, misuse, and addiction.

5.2 Risks to Patients with Serious Cardiac Disease

Sudden death has been reported in patients with structural cardiac abnormalities or other serious cardiac disease who were treated with CNS stimulants at the recommended ADHD dosage. Avoid ADDERALL XR use in patients with known structural cardiac abnormalities, cardiomyopathy, serious cardiac arrhythmia, coronary artery disease, or other serious cardiac disease.

5.3 Increased Blood Pressure and Heart Rate

CNS stimulants may cause an increase in blood pressure (mean increase approximately 2 to 4 mmHg) and heart rate (mean increase approximately 3 to 6 bpm).

Monitor all ADDERALL XR-treated patients for hypertension and tachycardia.

5.4 Psychiatric Adverse Reactions

Exacerbation of Pre-Existing Psychosis

Administration of stimulants may exacerbate symptoms of behavior disturbance and thought disorder in patients with pre-existing psychotic disorder.

Induction of a Manic Episode in Patients with Bipolar Disease

CNS stimulants may induce a manic or mixed episode in patients. Prior to initiating ADDERALL XR treatment, screen patients for risk factors for developing a manic episode (e.g., comorbid or history of depressive symptoms or a family history of suicide, bipolar disorder, or depression).

New Psychotic or Manic Symptoms

CNS stimulants, at the recommended dosage, may cause psychotic or manic symptoms (e.g., hallucinations, delusional thinking, or mania) in patients without a prior history of psychotic illness or mania. In a pooled analysis of multiple short-term, placebo-controlled studies of CNS stimulants, psychotic or manic symptoms occurred in approximately 0.1% of CNS stimulant-treated patients compared to 0% of placebo-treated patients. If such symptoms occur, consider discontinuing ADDERALL XR.

5.5 Long-Term Suppression of Growth in Pediatric Patients

ADDERALL XR is not approved for use and is not recommended in pediatric patients below 6 years of age [see Use in Specific Populations (8.4)].

CNS stimulants have been associated with weight loss and slowing of growth rate in pediatric patients. Closely monitor growth (weight and height) in ADDERALL XR-treated pediatric patients treated with CNS stimulants.

In a controlled trial of ADDERALL XR in adolescents, mean weight change from baseline within the initial 4 weeks of therapy was -1.1 lbs. and -2.8 lbs., respectively, for patients receiving 10 mg and 20 mg ADDERALL XR. Higher doses were associated with greater weight loss within the initial 4 weeks of treatment. Chronic use of amphetamines can be expected to cause a similar suppression of growth [see Adverse Reactions (6.1)].

Pediatric patients who are not growing or gaining weight as expected may need to have their treatment interrupted.

5.6 Seizures

There is some clinical evidence that stimulants may lower the convulsive threshold in patients with prior history of seizures, in patients with prior EEG abnormalities in the absence of seizures, and very rarely, in patients without a history of seizures and no prior EEG evidence of seizures. In the presence of seizures, ADDERALL XR should be discontinued.

5.7 Peripheral Vasculopathy, including Raynaud’s Phenomenon

CNS stimulants, including ADDERALL XR, used to treat ADHD are associated with peripheral vasculopathy, including Raynaud’s phenomenon. Signs and symptoms are usually intermittent and mild; however, sequelae have included digital ulceration and/or soft tissue breakdown. Effects of peripheral vasculopathy, including Raynaud’s phenomenon, were observed in postmarketing reports and at the therapeutic dosage of CNS stimulants in all age groups throughout the course of treatment. Signs and symptoms generally improved after dosage reduction or discontinuation of the CNS stimulant.

Careful observation for digital changes is necessary during ADDERALL XR treatment. Further clinical evaluation (e.g., rheumatology referral) may be appropriate for ADDERALL XR-treated patients who develop signs or symptoms of peripheral vasculopathy.

5.8 Serotonin Syndrome

Serotonin syndrome, a potentially life-threatening reaction, may occur when amphetamines are used in combination with other drugs that affect the serotonergic neurotransmitter systems such as MAOIs, selective serotonin reuptake inhibitors (SSRIs), serotonin norepinephrine reuptake inhibitors (SNRIs), triptans, tricyclic antidepressants, fentanyl, lithium, tramadol, tryptophan, buspirone, and St. John’s Wort [see Drug Interactions (7.1)]. Amphetamines and amphetamine derivatives are known to be metabolized, to some degree, by cytochrome P450 2D6 (CYP2D6) and display minor inhibition of CYP2D6 metabolism [see Clinical Pharmacology (12.3)]. The potential for a pharmacokinetic interaction exists with the coadministration of CYP2D6 inhibitors which may increase the risk with increased exposure to ADDERALL XR. In these situations, consider an alternative nonserotonergic drug or an alternative drug that does not inhibit CYP2D6 [see Drug Interactions (7.1)]. Serotonin syndrome symptoms may include mental status changes (e.g., agitation, hallucinations, delirium, and coma), autonomic instability (e.g., tachycardia, labile blood pressure, dizziness, diaphoresis, flushing, hyperthermia), neuromuscular symptoms (e.g., tremor, rigidity, myoclonus, hyperreflexia, incoordination), seizures, and/or gastrointestinal symptoms (e.g., nausea, vomiting, diarrhea).

Concomitant use of ADDERALL XR with MAOI drugs is contraindicated [see Contraindications (4)].

Discontinue treatment with ADDERALL XR and any concomitant serotonergic agents immediately if symptoms of serotonin syndrome occur, and initiate supportive symptomatic treatment. Concomitant use of ADDERALL XR with other serotonergic drugs or CYP2D6 inhibitors should be used only if the potential benefit justifies the potential risk. If clinically warranted, consider initiating ADDERALL XR with lower doses, monitoring patients for the emergence of serotonin syndrome during drug initiation or titration, and informing patients of the increased risk for serotonin syndrome.

5.9 Motor and Verbal Tics, and Worsening of Tourette’s Syndrome

CNS stimulants, including amphetamine, have been associated with the onset or exacerbation of motor and verbal tics. Worsening of Tourette’s syndrome has also been reported [see Adverse Reactions (6.2)].

Before initiating ADDERALL XR, assess the family history and clinically evaluate patients for tics or Tourette’s syndrome. Regularly monitor ADDERALL XR-treated patients for the emergence or worsening of tics or Tourette’s syndrome, and discontinue treatment if clinically appropriate.

6 ADVERSE REACTIONS

The following adverse reactions are discussed in greater detail in other sections of the labeling:

- Abuse, Misuse, and Addiction [see Boxed Warning, Warnings and Precautions (5.1), Drug Abuse and Dependence (9.2, 9.3)]
- Risks to Patients with Serious Cardiac Disease [see Warnings and Precautions (5.2)]
- Increased Blood Pressure and Heart Rate [see Warnings and Precautions (5.3)]
- Psychiatric Adverse Reactions [see Warnings and Precautions (5.4)]
- Long-Term Suppression of Growth in Pediatric Patients [see Warnings and Precautions (5.5)]
- Seizures [see Warnings and Precautions (5.6)]
- Peripheral Vasculopathy, including Raynaud’s Phenomenon [see Warnings and Precautions (5.7)]
- Serotonin Syndrome [see Warnings and Precautions (5.8)]
- Motor and Verbal Tics, and Worsening of Tourette’s Syndrome [see Warnings and Precautions (5.9)]

6.1 Clinical Trials Experience

Because clinical trials are conducted under widely varying conditions, adverse reaction rates observed in the clinical trials of a drug cannot be directly compared to rates in the clinical trials of another drug and may not reflect the rates observed in practice.

The premarketing development program for ADDERALL XR included exposures in a total of 1,315 participants in clinical trials (635 pediatric patients, 350 adolescent patients, 248 adult patients, and 82 healthy adult subjects). Of these, 635 patients (ages 6 to 12) were evaluated in two controlled clinical studies, one open-label clinical study, and two single-dose clinical pharmacology studies (N=40). Safety data on all patients are included in the discussion that follows. Adverse reactions were assessed by collecting adverse reactions, results of physical examinations, vital signs, weights, laboratory analyses, and ECGs.

Adverse reactions during exposure were obtained primarily by general inquiry and recorded by clinical investigators using terminology of their own choosing. Consequently, it is not possible to provide a meaningful estimate of the proportion of individuals experiencing adverse reactions without first grouping similar types of reactions into a smaller number of standardized event categories. In the tables and listings that follow, COSTART terminology has been used to classify reported adverse reactions.

The stated frequencies of adverse reactions represent the proportion of individuals who experienced, at least once, a treatment-emergent adverse event of the type listed.

Adverse Reactions Leading to Discontinuation of Treatment

In two placebo-controlled studies of up to 5 weeks duration among children with ADHD, 2.4% (10/425) of ADDERALL XR-treated patients discontinued due to adverse reactions (including three patients with loss of appetite, one of whom also reported insomnia) compared to 2.7% (7/259) receiving placebo.

The most frequent adverse reactions leading to discontinuation of ADDERALL XR in controlled and uncontrolled, multiple-dose clinical trials of children (N=595) were anorexia (loss of appetite) (2.9%), insomnia (1.5%), weight loss (1.2%), emotional lability (1%), and depression (0.7%). Over half of these patients were exposed to ADDERALL XR for 12 months or more.

In a separate placebo-controlled 4 week study in adolescents with ADHD, five patients (2.1%) discontinued treatment due to adverse events among ADDERALL XR-treated patients (N=233) compared to none who received placebo (N=54). The most frequent adverse event leading to discontinuation and considered to be drug-related (i.e., leading to discontinuation in at least 1% of ADDERALL XR-treated patients and at a rate at least twice that of placebo) was insomnia (1.3%, n=3).

In one placebo-controlled 4 week study among adults with ADHD with doses 20 to 60 mg, 23 patients (12.0%) discontinued treatment due to adverse events among ADDERALL XR-treated patients (N=191) compared to one patient (1.6%) who received placebo (N=64). The most frequent adverse events leading to discontinuation and considered to be drug-related (i.e., leading to discontinuation in at least 1% of ADDERALL XR-treated patients and at a rate at least twice that of placebo) were insomnia (5.2%, n=10), anxiety (2.1%, n=4), nervousness (1.6%, n=3), dry mouth (1.6%, n=3), anorexia (1.6%, n=3), tachycardia (1.6%, n=3), headache (1.6%, n=3), and asthenia (1.0%, n=2).

Adverse Reactions Occurring in Controlled Trials

Adverse reactions reported in a 3 week clinical trial of children and a 4 week clinical trial in adolescents and adults, respectively, treated with ADDERALL XR or placebo are presented in the tables below.

Table 1: Adverse Reactions Reported by 2% or More of Children (6 to 12 Years Old) Receiving ADDERALL XR with Higher Incidence than on Placebo in a 584 Patient Clinical Study
Body System | Preferred Term | ADDERALL XR (n=374) | Placebo (n=210)
General | Abdominal Pain (stomachache) Fever Infection Accidental Injury Asthenia (fatigue) | 14% 5% 4% 3% 2% | 10% 2% 2% 2% 0%
Digestive System | Loss of Appetite Vomiting Nausea Dyspepsia | 22% 7% 5% 2% | 2% 4% 3% 1%
Nervous System | Insomnia Emotional Lability Nervousness Dizziness | 17% 9% 6% 2% | 2% 2% 2% 0%
Metabolic/Nutritional | Weight Loss | 4% | 0%

Table 2: Adverse Reactions Reported by 5% or More of Adolescents (13 to 17 Years Old) Weighing ≤75 kg/165 lbs Receiving ADDERALL XR with Higher Incidence than Placebo in a 287 Patient Clinical Forced Weekly-Dose Titration Study [Included doses up to 40 mg.]
Body System | Preferred Term | ADDERALL XR (n=233) | Placebo (n=54)
General | Abdominal Pain (stomachache) | 11% | 2%
Digestive System | Loss of Appetite [Dose-related adverse reactions.] | 36% | 2%
Nervous System | Insomnia | 12% | 4%
 | Nervousness | 6% | 6% [Appears the same due to rounding.]
Metabolic/Nutritional | Weight Loss | 9% | 0%
Note: The following reactions did not meet the criterion for inclusion in Table 2 but were reported by 2 to 4% of adolescent patients receiving ADDERALL XR with a higher incidence than patients receiving placebo in this study: accidental injury, asthenia (fatigue), dry mouth, dyspepsia, emotional lability, nausea, somnolence, and vomiting.

Table 3: Adverse Reactions Reported by 5% or More of Adults Receiving ADDERALL XR with Higher Incidence than on Placebo in a 255 Patient Clinical Forced Weekly-Dose Titration Study [Included doses up to 60 mg.]
Body System | Preferred Term | ADDERALL XR (n=191) | Placebo (n=64)
General | Headache Asthenia | 26% 6% | 13% 5%
Digestive System | Dry Mouth Loss of Appetite Nausea Diarrhea | 35% 33% 8% 6% | 5% 3% 3% 0%
Nervous System | Insomnia Agitation Anxiety Dizziness Nervousness | 27% 8% 8% 7% 13% | 13% 5% 5% 0% 13% [Appears the same due to rounding.]
Cardiovascular System | Tachycardia | 6% | 3%
Metabolic/Nutritional | Weight Loss | 10% | 0%
Urogenital System | Urinary Tract Infection | 5% | 0%
Note: The following reactions did not meet the criterion for inclusion in Table 3 but were reported by 2 to 4% of adult patients receiving ADDERALL XR with a higher incidence than patients receiving placebo in this study: infection, photosensitivity reaction, constipation, tooth disorder (e.g., teeth clenching, tooth infection), emotional lability, libido decreased, somnolence, speech disorder (e.g., stuttering, excessive speech), palpitation, twitching, dyspnea, sweating, dysmenorrhea, and impotence.

Hypertension

In a controlled 4 week outpatient clinical study of adolescents with ADHD, isolated systolic blood pressure elevations ≥15 mmHg were observed in 7/64 (11%) placebo-treated patients and 7/100 (7%) patients receiving ADDERALL XR 10 or 20 mg. Isolated elevations in diastolic blood pressure ≥8 mmHg were observed in 16/64 (25%) placebo-treated patients and 22/100 (22%) ADDERALL XR-treated patients. Similar results were observed at higher doses [see Warnings and Precautions (5.2)].

In a single-dose pharmacokinetic study in 23 adolescents with ADHD, isolated increases in systolic blood pressure (above the upper 95% CI for age, gender, and stature) were observed in 2/17 (12%) and 8/23 (35%), subjects administered 10 and 20 mg ADDERALL XR, respectively. Higher single doses were associated with a greater increase in systolic blood pressure. All increases were transient, appeared maximal at 2 to 4 hours postdose and, not associated with symptoms.

6.2 Adverse Reactions Associated with the Use of Amphetamine, ADDERALL XR, or Adderall

The following adverse reactions have been identified during postapproval use of amphetamine, ADDERALL XR, or Adderall. Because these reactions are reported voluntarily from a population of uncertain size, it is not always possible to reliably estimate their frequency or establish a causal relationship to drug exposure.

Allergic: Urticaria, rash, hypersensitivity reactions including angioedema and anaphylaxis. Serious skin rashes, including Stevens-Johnson syndrome and toxic epidermal necrolysis have been reported.

Cardiovascular: Palpitations. There have been isolated reports of cardiomyopathy associated with chronic amphetamine use.

Central Nervous System: Psychotic episodes at recommended doses, overstimulation, restlessness, irritability, euphoria, dyskinesia, dysphoria, depression, tremor, motor and verbal tics, aggression, anger, logorrhea, dermatillomania, paresthesia (including formication), and bruxism.

Endocrine: Impotence, changes in libido, frequent or prolonged erections.

Eye Disorders: Vision blurred, mydriasis.

Gastrointestinal: Unpleasant taste, constipation, intestinal ischemia, and other gastrointestinal disturbances.

Musculoskeletal and Connective Tissue Disorders: Rhabdomyolysis.

Skin: Alopecia.

Vascular Disorders: Raynaud’s phenomenon.

7 DRUG INTERACTIONS

7.1 Clinically Important Interactions with Amphetamines

Table 4: Drugs Having Clinically Important Interactions with Amphetamines
Monoamine Oxidase Inhibitors (MAOIs)
Clinical Impact | Concomitant use of MAOIs and CNS stimulants can cause hypertensive crisis. Potential outcomes include death, stroke, myocardial infarction, aortic dissection, ophthalmological complications, eclampsia, pulmonary edema, and renal failure.
Intervention | Do not administer ADDERALL XR concomitantly or within 14 days after discontinuing MAOI [see Contraindications (4)].
Serotonergic Drugs
Clinical Impact | The concomitant use of ADDERALL XR and serotonergic drugs increases the risk of serotonin syndrome.
Intervention | Initiate with lower doses and monitor patients for signs and symptoms of serotonin syndrome, particularly during ADDERALL XR initiation or dosage increase. If serotonin syndrome occurs, discontinue ADDERALL XR and the concomitant serotonergic drug(s) [see Warnings and Precautions (5.8)].
CYP2D6 Inhibitors
Clinical Impact | The concomitant use of ADDERALL XR and CYP2D6 inhibitors may increase the exposure of ADDERALL XR compared to the use of the drug alone and increase the risk of serotonin syndrome.
Intervention | Initiate with lower doses and monitor patients for signs and symptoms of serotonin syndrome particularly during ADDERALL XR initiation and after a dosage increase. If serotonin syndrome occurs, discontinue ADDERALL XR and the CYP2D6 inhibitor [see Warnings and Precautions (5.8), Overdosage (10)].
Alkalinizing Agents
Clinical Impact | Increase blood levels and potentiate the action of amphetamine.
Intervention | Coadministration of ADDERALL XR and gastrointestinal or urinary alkalinizing agents should be avoided.
Acidifying Agents
Clinical Impact | Lower blood levels and efficacy of amphetamines.
Intervention | Increase dose based on clinical response.
Tricyclic Antidepressants
Clinical Impact | May enhance the activity of tricyclic or sympathomimetic agents causing striking and sustained increases in the concentration of d-amphetamine in the brain; cardiovascular effects can be potentiated.
Intervention | Monitor frequently and adjust or use alternative therapy based on clinical response.
Proton Pump Inhibitors
Clinical Impact | Time to maximum concentration (Tmax) of amphetamine is decreased compared to when administered alone.
Intervention | Monitor patients for changes in clinical effect and adjust therapy based on clinical response.

7.2 Drug-Laboratory Test Interactions

Amphetamines can cause a significant elevation in plasma corticosteroid levels. This increase is greatest in the evening. Amphetamines may interfere with urinary steroid determinations.

8 USE IN SPECIFIC POPULATIONS

8.1 Pregnancy

Pregnancy Exposure Registry

There is a pregnancy exposure registry that monitors pregnancy outcomes in women exposed to ADDERALL XR during pregnancy. Healthcare providers are encouraged to register patients by calling the National Pregnancy Registry for Psychostimulants at 1-866-961-2388 or visiting online at https://womensmentalhealth.org/clinical-and-research-programs/pregnancyregistry/othermedications/.

Risk Summary

Available data from published epidemiologic studies and postmarketing reports on use of prescription amphetamine in pregnant women have not identified a drug-associated risk of major birth defects and miscarriage (see Data). Adverse pregnancy outcomes, including premature delivery and low birth weight, have been seen in infants born to mothers taking amphetamines during pregnancy (see Clinical Considerations).

No apparent effects on morphological development were observed in embryo-fetal development studies, with oral administration of amphetamine to rats and rabbits during organogenesis at doses 2 and 12 times, respectively, the maximum recommended human dose (MRHD) of 20 mg/day given to adolescents, on a mg/m^2 basis. However, in a pre- and postnatal development study, amphetamine (d- to l- ratio of 3:1) administered orally to pregnant rats during gestation and lactation caused a decrease in pup survival and a decrease in pup body weight that correlated with a delay in developmental landmarks at clinically relevant doses of amphetamine. In addition, adverse effects on reproductive performance were observed in pups whose mothers were treated with amphetamine. Long-term neurochemical and behavioral effects have also been reported in animal developmental studies using clinically relevant doses of amphetamine (see Data).

The estimated background risk of major birth defects and miscarriage for the indicated population is unknown. All pregnancies have a background risk of birth defect, loss, or other adverse outcomes. In the U.S. general population, the estimated background risk of major birth defects and miscarriage in clinically recognized pregnancies is 2 to 4% and 15 to 20%, respectively.

Clinical Considerations

Fetal/Neonatal Adverse Reactions

Amphetamines, such as ADDERALL XR, cause vasoconstriction and thereby may decrease placental perfusion. In addition, amphetamines can stimulate uterine contractions, increasing the risk of premature delivery. Infants born to mothers taking amphetamines during pregnancy have an increased risk of premature delivery and low birth weight.

Monitor infants born to mothers taking amphetamines for symptoms of withdrawal such as feeding difficulties, irritability, agitation, and excessive drowsiness.

Data

Animal Data

Amphetamine (d- to l- enantiomer ratio of 3:1) had no apparent effects on embryofetal morphological development or survival when administered orally to pregnant rats and rabbits throughout the period of organogenesis at doses of up to 6 and 16 mg/kg/day, respectively. These doses are approximately 2 and 12 times, respectively, the maximum recommended human dose (MRHD) of 20 mg/day given to adolescents, on a mg/m^2 basis. Fetal malformations and death have been reported in mice following parenteral administration of d-amphetamine doses of 50 mg/kg/day (approximately 10 times the MRHD given to adolescents on a mg/m^2 basis) or greater to pregnant animals. Administration of these doses was also associated with severe maternal toxicity.

A study was conducted in which pregnant rats received daily oral doses of amphetamine (d- to l- enantiomer ratio of 3:1) of 2, 6, and 10 mg/kg from gestation Day 6 to lactation Day 20. These doses are approximately 0.8, 2, and 4 times the MRHD of 20 mg/day given to adolescents, on a mg/m^2 basis. All doses caused hyperactivity and decreased weight gain in the dams. A decrease in pup survival was seen at all doses. A decrease in pup body weight was seen at 6 and 10 mg/kg which correlated with delays in developmental landmarks, such as preputial separation and vaginal opening. Increased pup locomotor activity was seen at 10 mg/kg on Day 22 postpartum but not at 5 weeks postweaning. When pups were tested for reproductive performance at maturation, gestational weight gain, number of implantations, and number of delivered pups were decreased in the group whose mothers had been given 10 mg/kg.

A number of studies from the literature in rodents indicate that prenatal or early postnatal exposure to amphetamine (d- or d, l-) at doses similar to those used clinically can result in long-term neurochemical and behavioral alterations. Reported behavioral effects include learning and memory deficits, altered locomotor activity, and changes in sexual function.

8.2 Lactation

Risk Summary

Based on limited case reports in published literature, amphetamine (d- or d, l-) is present in human milk, at relative infant doses of 2 to 13.8% of the maternal weight-adjusted dosage and a milk/plasma ratio ranging between 1.9 and 7.5. There are no reports of adverse effects on the breastfed infant. Long-term neurodevelopmental effects on infants from amphetamine exposure are unknown. It is possible that large dosages of amphetamine might interfere with milk production, especially in women whose lactation is not well established. Because of the potential for serious adverse reactions in nursing infants, advise patients that breastfeeding is not recommended during treatment with ADDERALL XR.

8.4 Pediatric Use

The safety and effectiveness of ADDERALL XR have not been established in pediatric patients less than 6 years of age.

The safety and effectiveness of ADDERALL XR have been established in pediatric patients with ADHD 6 years of age and older.

In studies evaluating extended-release amphetamine products, patients 4 to <6 years of age had higher systemic amphetamine exposures than those observed in older pediatric patients at the same dosage. Pediatric patients 4 to <6 years of age also had a higher incidence of adverse reactions, including weight loss.

Long-Term Growth Suppression

Growth should be monitored during treatment with stimulants, including ADDERALL XR, and pediatric patients aged 6 to 17 years who are not growing or gaining weight as expected may need to have their treatment interrupted [see Warnings and Precautions (5.5)].

Juvenile Animal Toxicity Data

Juvenile rats treated with mixed amphetamine salts early in the postnatal period through sexual maturation demonstrated transient changes in motor activity. Learning and memory was impaired at approximately 6 times the maximum recommended human dose (MRHD) given to children on a mg/m^2 basis. No recovery was seen following a drug-free period. A delay in sexual maturation was observed at a dose approximately 6 times the MRHD given to children on a mg/m^2 basis, although there was no effect on fertility.

In a juvenile developmental study, rats received daily oral doses of amphetamine (d to l enantiomer ratio of 3:1) of 2, 6, or 20 mg/kg on Days 7 to 13 of age; from Day 14 to approximately Day 60 of age these doses were given b.i.d. for total daily doses of 4, 12, or 40 mg/kg. The latter doses are approximately 0.6, 2, and 6 times the MRHD of 30 mg/day, given to children on a mg/m^2 basis. Postdosing hyperactivity was seen at all doses; motor activity measured prior to the daily dose was decreased during the dosing period but the decreased motor activity was largely absent after an 18 day drug-free recovery period. Performance in the Morris water maze test for learning and memory was impaired at the 40 mg/kg dose, and sporadically at the lower doses, when measured prior to the daily dose during the treatment period; no recovery was seen after a 19 day drug-free period. A delay in the developmental milestones of vaginal opening and preputial separation was seen at 40 mg/kg but there was no effect on fertility.

8.5 Geriatric Use

ADDERALL XR has not been studied in the geriatric population.

8.6 Renal Impairment

Due to reduced clearance of amphetamines in patients with severe renal impairment (GFR 15 to <30 mL/min/1.73 m^2), the recommended dose should be reduced. ADDERALL XR is not recommended in patients with ESRD (GFR <15 mL/min/1.73 m^2) [see Dosage and Administration (2.6), Clinical Pharmacology (12.3)].

d-Amphetamine is not dialyzable.

9 DRUG ABUSE AND DEPENDENCE

9.1 Controlled Substance

ADDERALL XR contains amphetamine, a Schedule II controlled substance.

9.2 Abuse

ADDERALL XR has a high potential for abuse and misuse which can lead to the development of a substance use disorder, including addiction [see Warnings and Precautions (5.1)]. ADDERALL XR can be diverted for non-medical use into illicit channels or distribution.

Abuse is the intentional non-therapeutic use of a drug, even once, to achieve a desired psychological or physiological effect. Misuse is the intentional use, for therapeutic purposes, of a drug by an individual in a way other than prescribed by a healthcare provider or for whom it was not prescribed. Drug addiction is a cluster of behavioral, cognitive, and physiological phenomena that may include a strong desire to take the drug, difficulties in controlling drug use (e.g., continuing drug use despite harmful consequences, giving a higher priority to drug use than other activities and obligations), and possible tolerance or physical dependence.

Misuse and abuse of amphetamine may cause increased heart rate, respiratory rate, or blood pressure; sweating; dilated pupils; hyperactivity; restlessness; insomnia; decreased appetite; loss of coordination; tremors; flushed skin; vomiting; and/or abdominal pain. Anxiety, psychosis, hostility, aggression, and suicidal or homicidal ideation have also been observed with CNS stimulants abuse and/or misuse. Misuse and abuse of CNS stimulants, including ADDERALL XR, can result in overdose and death [see Overdosage (10)], and this risk is increased with higher doses or unapproved methods of administration, such as snorting or injection.

9.3 Dependence

Physical Dependence

ADDERALL XR may produce physical dependence. Physical dependence is a state that develops as a result of physiological adaptation in response to repeated drug use, manifested by withdrawal signs and symptoms after abrupt discontinuation or a significant dose reduction of a drug.

Withdrawal signs and symptoms after abrupt discontinuation or dose reduction following prolonged use of CNS stimulants including ADDERALL XR include dysphoric mood; depression; fatigue; vivid, unpleasant dreams; insomnia or hypersomnia; increased appetite; and psychomotor retardation or agitation.

Tolerance

ADDERALL XR may produce tolerance. Tolerance is a physiological state characterized by a reduced response to a drug after repeated administration (i.e., a higher dose of a drug is required to produce the same effect that was once obtained at a lower dose).

10 OVERDOSAGE

Clinical Effects of Overdose

Overdose of CNS stimulants is characterized by the following sympathomimetic effects:

- Cardiovascular effects including tachyarrhythmias, and hypertension or hypotension. Vasospasm, myocardial infarction, or aortic dissection may precipitate sudden cardiac death. Takotsubo cardiomyopathy may develop.
- CNS effects including psychomotor agitation, confusion, and hallucinations. Serotonin syndrome, seizures, cerebral vascular accidents, and coma may occur.
- Life-threatening hyperthermia (temperatures greater than 104°F) and rhabdomyolysis may develop.

Overdose Management

Consider the possibility of multiple drug ingestion. The pharmacokinetic profile of ADDERALL XR should be considered when treating patients with overdose. D-amphetamine is not dialyzable. Consider contacting the Poison Help line (1-800-222-1222) or a medical toxicologist for additional overdose management recommendations.

11 DESCRIPTION

ADDERALL XR extended-release capsules contain mixed salts of a single-entity amphetamine, a CNS stimulant. ADDERALL XR contains equal amounts (by weight) of four salts: dextroamphetamine sulfate, amphetamine sulfate, dextroamphetamine saccharate and amphetamine (D, L)-aspartate monohydrate. This results in a 3.1:1 mixture of dextro- to levo-amphetamine base equivalent.

The 5 mg, 10 mg, 15 mg, 20 mg, 25 mg, and 30 mg strength extended-release capsules are for oral administration. ADDERALL XR contains two types of drug-containing beads (immediate-release and delayed-release) which prolong the release of amphetamine compared to the Adderall (immediate-release) tablet formulation.

Each capsule contains:

Capsule Strength | 5 mg | 10 mg | 15 mg | 20 mg | 25 mg | 30 mg
Dextroamphetamine Saccharate | 1.25 mg | 2.5 mg | 3.75 mg | 5.0 mg | 6.25 mg | 7.5 mg
Amphetamine (D,L)-Aspartate Monohydrate | 1.25 mg | 2.5 mg | 3.75 mg | 5.0 mg | 6.25 mg | 7.5 mg
Dextroamphetamine Sulfate | 1.25 mg | 2.5 mg | 3.75 mg | 5.0 mg | 6.25 mg | 7.5 mg
Amphetamine Sulfate | 1.25 mg | 2.5 mg | 3.75 mg | 5.0 mg | 6.25 mg | 7.5 mg
Total amphetamine base equivalence | 3.1 mg | 6.3 mg | 9.4 mg | 12.5 mg | 15.6 mg | 18.8 mg
d-amphetamine base equivalence | 2.4 mg | 4.7 mg | 7.1 mg | 9.5 mg | 11.9 mg | 14.2 mg
l-amphetamine base equivalence | 0.75 mg | 1.5 mg | 2.3 mg | 3.0 mg | 3.8 mg | 4.5 mg

Inactive Ingredients and Colors

The inactive ingredients in ADDERALL XR extended-release capsules include: gelatin capsules, hydroxypropyl methylcellulose, methacrylic acid copolymer, Opadry® beige, sugar spheres, talc, and triethyl citrate. Gelatin capsules contain edible inks, kosher gelatin, and titanium dioxide. The 5 mg, 10 mg, and 15 mg capsules also contain FD&C Blue #2. The 20 mg, 25 mg, and 30 mg capsules also contain red iron oxide and yellow iron oxide.

12 CLINICAL PHARMACOLOGY

12.1 Mechanism of Action

Amphetamines are non-catecholamine sympathomimetic amines with CNS stimulant activity. The mode of therapeutic action in ADHD is not known.

12.2 Pharmacodynamics

Amphetamines block the reuptake of norepinephrine and dopamine into the presynaptic neuron and increase the release of these monoamines into the extraneuronal space.

12.3 Pharmacokinetics

Pharmacokinetic studies of ADDERALL XR have been conducted in healthy adult and pediatric (children aged 6 to 12 yrs) subjects, adolescent (13 to 17 yrs), and children with ADHD. Both Adderall (immediate-release) tablets and ADDERALL XR extended-release capsules contain d-amphetamine and l-amphetamine salts in the ratio of 3:1. Following administration of Adderall (immediate-release), the peak plasma concentrations occurred in about 3 hours for both d-amphetamine and l-amphetamine.

The time to reach maximum plasma concentration (Tmax) for ADDERALL XR is about 7 hours, which is about 4 hours longer compared to Adderall (immediate-release). This is consistent with the extended-release nature of the product.

Figure 1: Mean d-amphetamine and l-amphetamine Plasma Concentrations Following Administration of ADDERALL XR 20 mg (8 am) and Adderall (immediate-release) 10 mg Twice Daily (8 am and 12 noon) in the Fed State.

A single dose of ADDERALL XR 20 mg extended-release capsules provided comparable plasma concentration profiles of both d-amphetamine and l-amphetamine to Adderall (immediate-release) 10 mg twice daily administered 4 hours apart.

The mean elimination half-life for d-amphetamine is 10 hours in adults; 11 hours in adolescents aged 13 to 17 years and weighing less than or equal to 75 kg/165 lbs; and 9 hours in children aged 6 to 12 years. For the l-amphetamine, the mean elimination half-life in adults is 13 hours; 13 to 14 hours in adolescents; and 11 hours in children aged 6 to 12 years. On a mg/kg body weight basis, children have a higher clearance than adolescents or adults (see Special Populations).

ADDERALL XR demonstrates linear pharmacokinetics over the dose range of 20 to 60 mg in adults and adolescents weighing greater than 75 kg/165 lbs, over the dose range of 10 to 40 mg in adolescents weighing less than or equal to 75 kg/165 lbs, and 5 to 30 mg in children aged 6 to 12 years. There is no unexpected accumulation at steady state in children.

Food does not affect the extent of absorption of d-amphetamine and l-amphetamine, but prolongs Tmax by 2.5 hours (from 5.2 hrs at fasted state to 7.7 hrs after a high-fat meal) for d-amphetamine and 2.7 hours (from 5.6 hrs at fasted state to 8.3 hrs after a high-fat meal) for l-amphetamine after administration of ADDERALL XR 30 mg. Opening the capsule and sprinkling the contents on applesauce results in comparable absorption to the intact capsule taken in the fasted state. Equal doses of ADDERALL XR strengths are bioequivalent.

Metabolism and Excretion

Amphetamine is reported to be oxidized at the 4 position of the benzene ring to form 4-hydroxyamphetamine, or on the side chain α or β carbons to form alpha-hydroxy-amphetamine or norephedrine, respectively. Norephedrine and 4-hydroxy-amphetamine are both active and each is subsequently oxidized to form 4-hydroxy-norephedrine. Alpha-hydroxy-amphetamine undergoes deamination to form phenylacetone, which ultimately forms benzoic acid and its glucuronide and the glycine conjugate hippuric acid. Although the enzymes involved in amphetamine metabolism have not been clearly defined, CYP2D6 is known to be involved with formation of 4-hydroxy-amphetamine. Since CYP2D6 is genetically polymorphic, population variations in amphetamine metabolism are a possibility.

Amphetamine is known to inhibit monoamine oxidase, whereas the ability of amphetamine and its metabolites to inhibit various P450 isozymes and other enzymes has not been adequately elucidated. In vitro experiments with human microsomes indicate minor inhibition of CYP2D6 by amphetamine and minor inhibition of CYP1A2, 2D6, and 3A4 by one or more metabolites. However, due to the probability of auto-inhibition and the lack of information on the concentration of these metabolites relative to in vivo concentrations, no predications regarding the potential for amphetamine or its metabolites to inhibit the metabolism of other drugs by CYP isozymes in vivo can be made.

With normal urine pHs, approximately half of an administered dose of amphetamine is recoverable in urine as derivatives of alpha-hydroxy-amphetamine and approximately another 30 to 40% of the dose is recoverable in urine as amphetamine itself. Since amphetamine has a pKa of 9.9, urinary recovery of amphetamine is highly dependent on pH and urine flow rates. Alkaline urine pHs result in less ionization and reduced renal elimination, and acidic pHs and high flow rates result in increased renal elimination with clearances greater than glomerular filtration rates, indicating the involvement of active secretion. Urinary recovery of amphetamine has been reported to range from 1 to 75%, depending on urinary pH, with the remaining fraction of the dose hepatically metabolized. Consequently, both hepatic and renal dysfunction have the potential to inhibit the elimination of amphetamine and result in prolonged exposures. In addition, drugs that effect urinary pH are known to alter the elimination of amphetamine, and any decrease in amphetamine's metabolism that might occur due to drug interactions or genetic polymorphisms is more likely to be clinically significant when renal elimination is decreased [see Drug Interactions (7)].

Special Populations

Comparison of the pharmacokinetics of d- and l-amphetamine after oral administration of ADDERALL XR in children (6 to 12 years) and adolescent (13 to 17 years) ADHD patients and healthy adult volunteers indicates that body weight is the primary determinant of apparent differences in the pharmacokinetics of d- and l-amphetamine across the age range. Systemic exposure measured by area under the curve to infinity (AUC∞) and maximum plasma concentration (Cmax) decreased with increases in body weight, while oral volume of distribution (VZ/F), oral clearance (CL/F), and elimination half-life (t1/2) increased with increases in body weight.

Pediatric Patients

On a mg/kg weight basis, children eliminated amphetamine faster than adults. The elimination half-life (t1/2) is approximately 1 hour shorter for d-amphetamine and 2 hours shorter for l-amphetamine in children than in adults. However, children had higher systemic exposure to amphetamine (Cmax and AUC) than adults for a given dose of ADDERALL XR, which was attributed to the higher dose administered to children on a mg/kg body weight basis compared to adults. Upon dose normalization on a mg/kg basis, children showed 30% less systemic exposure compared to adults.

Gender

Systemic exposure to amphetamine was 20 to 30% higher in women (N=20) than in men (N=20) due to the higher dose administered to women on a mg/kg body weight basis. When the exposure parameters (Cmax and AUC) were normalized by dose (mg/kg), these differences diminished. Age and gender had no direct effect on the pharmacokinetics of d- and l-amphetamine.

Race

Formal pharmacokinetic studies for race have not been conducted. However, amphetamine pharmacokinetics appeared to be comparable among Caucasians (N=33), Blacks (N=8), and Hispanics (N=10).

Patients with Renal Impairment

The effect of renal impairment on d- and l-amphetamine after administration of ADDERALL XR has not been studied. The impact of renal impairment on the disposition of amphetamine is expected to be similar between oral administration of lisdexamfetamine and ADDERALL XR.

In a pharmacokinetic study of lisdexamfetamine in adult subjects with normal and impaired renal function, mean d-amphetamine clearance was reduced from 0.7 L/hr/kg in normal subjects to 0.4 L/hr/kg in subjects with severe renal impairment (GFR 15 to <30 mL/min/1.73 m^2). Dialysis did not significantly affect the clearance of d-amphetamine [see Use in Specific Populations (8.6)].

13 NONCLINICAL TOXICOLOGY

13.1 Carcinogenesis, Mutagenesis, Impairment of Fertility

Carcinogenesis

No evidence of carcinogenicity was found in studies in which d, l-amphetamine (enantiomer ratio of 1:1) was administered to mice and rats in the diet for 2 years at doses of up to 30 mg/kg/day in male mice, 19 mg/kg/day in female mice, and 5 mg/kg/day in male and female rats. These doses are approximately 2.4, 1.5, and 0.8 times, respectively, the maximum recommended human dose of 30 mg/day given to children, on a mg/m^2 basis.

Mutagenesis

Amphetamine, in the enantiomer ratio d- to l- ratio of 3:1, was not clastogenic in the mouse bone marrow micronucleus test in vivo and was negative when tested in the E. coli component of the Ames test in vitro. d, l-Amphetamine (1:1 enantiomer ratio) has been reported to produce a positive response in the mouse bone marrow micronucleus test, an equivocal response in the Ames test, and negative responses in the in vitro sister chromatid exchange and chromosomal aberration assays.

Impairment of Fertility

Amphetamine, in the enantiomer ratio d- to l- ratio of 3:1, did not adversely affect fertility or early embryonic development in the rat at doses of up to 20 mg/kg/day (approximately 8 times the maximum recommended human dose of 20 mg/day given to adolescents, on a mg/m^2 basis).

13.2 Animal Toxicology and/or Pharmacology

Acute administration of high doses of amphetamine (d- or d, l-) has been shown to produce long-lasting neurotoxic effects, including irreversible nerve fiber damage in rodents. The significance of these findings to humans is unknown.

14 CLINICAL STUDIES

Pediatric Patients

A double-blind, randomized, placebo-controlled, parallel-group study was conducted in children aged 6 to 12 (N=584) who met DSM-IV® criteria for ADHD (either the combined type or the hyperactive-impulsive type). Patients were randomized to fixed-dose treatment groups receiving final doses of 10 mg, 20 mg, or 30 mg of ADDERALL XR or placebo once daily in the morning for three weeks. Significant improvements in patient behavior, based upon teacher ratings of attention and hyperactivity, were observed for all ADDERALL XR doses compared to patients who received placebo, for all three weeks, including the first week of treatment, when all ADDERALL XR subjects were receiving a dose of 10 mg/day. Patients who received ADDERALL XR showed behavioral improvements in both morning and afternoon assessments compared to patients on placebo.

In a classroom analogue study, patients (N=51) receiving fixed doses of 10 mg, 20 mg, or 30 mg ADDERALL XR demonstrated statistically significant improvements in teacher-rated behavior and performance measures, compared to patients treated with placebo.

A double-blind, randomized, multicenter, parallel-group, placebo-controlled study was conducted in adolescents aged 13 to 17 (N=327) who met DSM-IV® criteria for ADHD. The primary cohort of patients (n=287, weighing ≤75 kg/165 lbs) were randomized to fixed-dose treatment groups and received four weeks of treatment. Patients were randomized to receive final doses of 10 mg, 20 mg, 30 mg, and 40 mg ADDERALL XR or placebo once daily in the morning. Patients randomized to doses greater than 10 mg were titrated to their final doses by 10 mg each week. The secondary cohort consisted of 40 subjects weighing >75 kg/165 lbs who were randomized to fixed-dose treatment groups receiving final doses of 50 mg and 60 mg ADDERALL XR or placebo once daily in the morning for 4 weeks. The primary efficacy variable was the Attention Deficit Hyperactivity Disorder-Rating Scale IV (ADHD-RS-IV) total score for the primary cohort. The ADHD-RS-IV is an 18- item scale that measures the core symptoms of ADHD. Improvements in the primary cohort were statistically significantly greater in all four primary cohort active treatment groups (ADDERALL XR 10 mg, 20 mg, 30 mg, and 40 mg) compared with the placebo group. There was not adequate evidence that doses greater than 20 mg/day conferred additional benefit.

Adult Patients

A double-blind, randomized, placebo-controlled, parallel-group study was conducted in adults (N=255) who met DSM-IV® criteria for ADHD. Patients were randomized to fixed-dose treatment groups receiving final doses of 20 mg, 40 mg, or 60 mg of ADDERALL XR or placebo once daily in the morning for four weeks. Significant improvements, measured with the Attention Deficit Hyperactivity Disorder-Rating Scale (ADHD-RS), an 18-item scale that measures the core symptoms of ADHD, were observed at endpoint for all ADDERALL XR doses compared to patients who received placebo for all four weeks. There was not adequate evidence that doses greater than 20 mg/day conferred additional benefit.

16 HOW SUPPLIED/STORAGE AND HANDLING

ADDERALL XR 5 mg extended-release capsules: Clear/blue (imprinted ADDERALL XR 5 mg), bottles of 100, NDC 54092-381-01

ADDERALL XR 10 mg extended-release capsules: Blue/blue (imprinted ADDERALL XR 10 mg), bottles of 100, NDC 54092-383-01

ADDERALL XR 15 mg extended-release capsules: Blue/white (imprinted ADDERALL XR 15 mg), bottles of 100, NDC 54092-385-01

ADDERALL XR 20 mg extended-release capsules: Orange/orange (imprinted ADDERALL XR 20 mg), bottles of 100, NDC 54092-387-01

ADDERALL XR 25 mg extended-release capsules: Orange/white (imprinted ADDERALL XR 25 mg), bottles of 100, NDC 54092-389-01

ADDERALL XR 30 mg extended-release capsules: Natural/orange (imprinted ADDERALL XR 30 mg), bottles of 100, NDC 54092-391-01

STORAGE AND HANDLING

Dispense in a tight, light-resistant container as defined in the USP.

Store at room temperature, 20 to 25ºC (68 to 77ºF). Excursions permitted to 15 to 30ºC (59 to 86ºF) [see USP Controlled Room Temperature].

17 PATIENT COUNSELING INFORMATION

Advise the patient to read the FDA-approved patient labeling (Medication Guide).

Abuse, Misuse, and Addiction

Educate patients and their families about the risks of abuse, misuse, and addiction of ADDERALL XR, which can lead to overdose and death, and proper disposal of any unused drug [see Warnings and Precautions (5.1), Drug Abuse and Dependence (9.2), Overdosage (10)]. Advise patients to store ADDERALL XR in a safe place, preferably locked, and instruct patients to not give ADDERALL XR to anyone else.

Risks to Patients with Serious Cardiac Disease

Advise patients that there are potential risks to patients with serious cardiac disease, including sudden death, with ADDERALL XR use. Instruct patients to contact a healthcare provider immediately if they develop symptoms such as exertional chest pain, unexplained syncope, or other symptoms suggestive of cardiac disease [see Warnings and Precautions (5.2)].

Increased Blood Pressure and Heart Rate

Advise patients that ADDERALL XR can cause elevations in blood pressure and heart rate [see Warnings and Precautions (5.3)].

Psychiatric Adverse Reactions

Prior to initiating treatment with ADDERALL XR, adequately screen patients with comorbid depressive symptoms to determine if they are at risk for bipolar disorder. Such screening should include a detailed psychiatric history, including a family history of suicide, bipolar disorder, and/or depression. Additionally, ADDERALL XR therapy at usual doses may cause treatment-emergent psychotic or manic symptoms in patients without prior history of psychotic symptoms or mania [see Warnings and Precautions (5.4)].

Circulation Problems in Fingers and Toes [Peripheral Vasculopathy, including Raynaud’s Phenomenon]

Instruct patients beginning treatment with ADDERALL XR about the risk of peripheral vasculopathy, including Raynaud’s phenomenon, and in associated signs and symptoms: fingers or toes may feel numb, cool, painful, and/or may change color from pale, to blue, to red. Instruct patients to report to their physician any new numbness, pain, skin color change, or sensitivity to temperature in fingers or toes. Instruct patients to call their physician immediately with any signs of unexplained wounds appearing on fingers or toes while taking ADDERALL XR. Further clinical evaluation (e.g., rheumatology referral) may be appropriate for certain patients [see Warnings and Precautions (5.7)].

Serotonin Syndrome

Caution patients about the risk of serotonin syndrome with concomitant use of ADDERALL XR and other serotonergic drugs including SSRIs, SNRIs, triptans, tricyclic antidepressants, fentanyl, lithium, tramadol, tryptophan, buspirone, St. John’s Wort, and with drugs that impair metabolism of serotonin (in particular MAOIs, both those intended to treat psychiatric disorders and also others such as linezolid) [see Contraindications (4), Warnings and Precautions (5.8), Drug Interactions (7.1)]. Advise patients to contact their healthcare provider or report to the emergency room if they experience signs or symptoms of serotonin syndrome.

Concomitant Medications

Advise patients to notify their physicians if they are taking, or plan to take, any prescription or over-the-counter drugs because there is a potential for interactions [see Drug Interactions (7.1)].

Growth

Monitor growth in children during treatment with ADDERALL XR, and patients who are not growing or gaining weight as expected may need to have their treatment interrupted [see Warnings and Precautions (5.5)].

Motor and Verbal Tics, and Worsening of Tourette’s Syndrome

Advise patients that motor and verbal tics and worsening of Tourette’s syndrome may occur during treatment with ADDERALL XR. Instruct patients to notify their healthcare provider if emergence of new tics or worsening of tics or Tourette’s syndrome occurs [see Warnings and Precautions (5.9)].

Pregnancy Registry

Advise patients that there is a pregnancy exposure registry that monitors pregnancy outcomes in women exposed to ADDERALL XR during pregnancy [see Use in Specific Populations (8.1)].

Pregnancy

Advise patients to notify their healthcare provider if they become pregnant or intend to become pregnant during treatment with ADDERALL XR. Advise patients of the potential fetal effects from the use of ADDERALL XR during pregnancy [see Use in Specific Populations (8.1)].

Lactation

Advise women not to breastfeed if they are taking ADDERALL XR [see Use in Specific Populations (8.2)].

Distributed by:
Takeda Pharmaceuticals America, Inc.
Cambridge, MA 02142

For more information call 1-877-825-3327.

ADDERALL XR is a registered trademark of Takeda Pharmaceuticals U.S.A., Inc.

ADDERALL is a registered trademark of Takeda Pharmaceuticals U.S.A., Inc. under license to Duramed Pharmaceuticals, Inc.

OPADRY is a registered trademark of BPSI Holdings, LLC.

© 2025 Takeda Pharmaceuticals U.S.A., Inc. All rights reserved.

ADL364

MEDICATION GUIDE
ADDERALL XR® (ADD-ur-all X-R)
(mixed salts of a single-entity amphetamine product)
extended-release capsules, CII

What is the most important information I should know about ADDERALL XR?
ADDERALL XR may cause serious side effects, including:
Abuse, misuse, and addiction. ADDERALL XR has a high chance for abuse and misuse and may lead to substance use problems, including addiction. Misuse and abuse of ADDERALL XR, other amphetamine containing medicines, and methylphenidate containing medicines, can lead to overdose and death. The risk of overdose and death is increased with higher doses of ADDERALL XR or when it is used in ways that are not approved, such as snorting or injection.

- Your healthcare provider should check you or your child’s risk for abuse, misuse, and addiction before starting treatment with ADDERALL XR and will monitor you or your child during treatment.
- ADDERALL XR may lead to physical dependence after prolonged use, even if taken as directed by your healthcare provider.
- Do not give ADDERALL XR to anyone else. See “What is ADDERALL XR?” for more information.
- Keep ADDERALL XR in a safe place and properly dispose of any unused medicine. See “How should I store ADDERALL XR?” for more information.

Tell your healthcare provider if you or your child have ever abused or been dependent on alcohol, prescription medicines, or street drugs.

- Risks for people with serious heart disease. Sudden death has happened in people who have heart defects or other serious heart disease.

Your healthcare provider should check you or your child carefully for heart problems before starting treatment with ADDERALL XR. Tell your healthcare provider if you or your child have any heart problems, heart disease, or heart defects.

Call your healthcare provider or go to the nearest hospital emergency room right away if you or your child have any signs of heart problems such as chest pain, shortness of breath, or fainting during treatment with ADDERALL XR.

- Increased blood pressure and heart rate.
  Your healthcare provider should check you or your child’s blood pressure and heart rate regularly during treatment with ADDERALL XR.
- Mental (psychiatric) problems, including:
  - new or worse behavior or thought problems
  - new or worse bipolar illness
  - new psychotic symptoms (such as hearing voices, or seeing or believing things that are not real) or new manic symptoms

Tell your healthcare provider about any mental problems you or your child have or about a family history of suicide, bipolar illness, or depression.

Call your healthcare provider right away if you or your child have any new or worsening mental symptoms or problems during treatment with ADDERALL XR, especially hearing voices, seeing or believing things that are not real, or new manic symptoms.

What is ADDERALL XR?

ADDERALL XR is a central nervous system (CNS) stimulant prescription medicine used for the treatment of Attention Deficit Hyperactivity Disorder (ADHD) in adults and children 6 years of age and older. ADDERALL XR may help increase attention and decrease impulsiveness and hyperactivity in people with ADHD.

ADDERALL XR is not recommended for use in children under 6 years of age with ADHD.

ADDERALL XR is a federally controlled substance (CII) because it contains amphetamine that can be a target for people who abuse prescription medicines or street drugs. Keep ADDERALL XR in a safe place to protect it from theft. Never give your ADDERALL XR to anyone else because it may cause death or harm them. Selling or giving away ADDERALL XR may harm others and is against the law.

Do not take ADDERALL XR if you or your child:

- are taking or have taken within the past 14 days, a medicine used to treat depression called a monoamine oxidase inhibitor (MAOI), including the antibiotic linezolid or the intravenous medicine methylene blue.
- are allergic to amphetamine products or any of the ingredients in ADDERALL XR. See the end of this Medication Guide for a complete list of ingredients in ADDERALL XR.

Before taking ADDERALL XR tell your healthcare provider about all of your or your child’s medical conditions, including if you or your child:

- have heart problems, heart disease, heart defects, or high blood pressure
- have mental problems including psychosis, mania, bipolar illness, or depression, or have a family history of suicide, bipolar illness, or depression
- have kidney problems
- have seizures or have had an abnormal brain wave test (EEG)
- have circulation problems in fingers and toes
- have or had repeated movements or sounds (tics) or Tourette’s syndrome, or have a family history of tics or Tourette’s syndrome
- are pregnant or plan to become pregnant. It is not known if ADDERALL XR will harm the unborn baby. Tell your healthcare provider if you or your child become pregnant during treatment with ADDERALL XR.
  - There is a pregnancy registry for females who are exposed to ADDERALL XR during pregnancy. The purpose of the registry is to collect information about the health of females exposed to ADDERALL XR and their baby. If you or your child becomes pregnant during treatment with ADDERALL XR, talk to your healthcare provider about registering with the National Pregnancy Registry of Psychostimulants at 1-866-961-2388 or visit online at https://womensmentalhealth.org/clinical-and-research-programs/pregnancyregistry/othermedications/.
- are breastfeeding or plan to breastfeed. ADDERALL XR passes into breast milk. You or your child should not breastfeed during treatment with ADDERALL XR. Talk to your healthcare provider about the best way to feed the baby during treatment with ADDERALL XR.

Tell your healthcare provider about all of the medicines that you or your child take, including prescription and over-the-counter medicines, vitamins, and herbal supplements.

ADDERALL XR and some medicines may interact with each other and cause serious side effects. Sometimes the doses of other medicines will need to be changed during treatment with ADDERALL XR.

Your healthcare provider will decide if ADDERALL XR can be taken with other medicines.

Especially tell your healthcare provider if you or your child take:

- selective serotonin reuptake inhibitors (SSRIs)
- medicines used to treat migraine headaches called triptans
- lithium
- tramadol
- buspirone

- serotonin norepinephrine reuptake inhibitors (SNRIs)
- tricyclic antidepressants
- fentanyl
- tryptophan
- St. John’s Wort

Know the medicines that you or your child take. Keep a list of your or your child’s medicines with you to show your healthcare provider and pharmacist when you or your child get a new medicine.

Do not start any new medicine during treatment with ADDERALL XR without talking to your healthcare provider first.

How should ADDERALL XR be taken?

- Take ADDERALL XR exactly as prescribed by your or your child’s healthcare provider.
- Your healthcare provider may change the dose if needed.
- Take ADDERALL XR 1 time each day in the morning when you first wake up.
- ADDERALL XR can be taken with or without food.
- Swallow ADDERALL XR capsules whole. If you or your child cannot swallow the capsule whole, open it and sprinkle the medicine on applesauce.
  - Swallow all of the applesauce and medicine mixture right away.
  - Do not chew the applesauce and medicine mixture.
  - Do not store the applesauce sprinkled with ADDERALL XR.

If you or your child take too much ADDERALL XR, call your healthcare provider or Poison Help line at 1-800-222-1222 or go to the nearest hospital emergency room right away.

What are the possible side effects of ADDERALL XR?
ADDERALL XR may cause serious side effects, including:

- See "What is the most important information I should know about ADDERALL XR?"
- Slowing of growth (height and weight) in children. Children should have their height and weight checked often during treatment with ADDERALL XR. Your healthcare provider may stop your child’s ADDERALL XR treatment if they are not growing or gaining weight as expected.
- Seizures. Your healthcare provider may stop treatment with ADDERALL XR if you or your child have a seizure.
- Circulation problems in fingers and toes (peripheral vasculopathy, including Raynaud’s phenomenon).
  Signs and symptoms may include:
  - fingers or toes may feel numb, cool, painful
  - fingers or toes may change color from pale, to blue, to red
  Tell your healthcare provider if you have or your child have any numbness, pain, skin color change, or sensitivity to temperature in your fingers or toes.
  Call your healthcare provider right away if you have or your child have any signs of unexplained wounds appearing on fingers or toes during treatment with ADDERALL XR.

- Serotonin syndrome. This problem may happen when ADDERALL XR is taken with certain other medicines and may be life-threatening. Stop taking ADDERALL XR and call your healthcare provider or go to the nearest hospital emergency room right away if you or your child develop any of the following signs and symptoms of serotonin syndrome:

- agitation, hallucinations, coma, or other changes in mental status
- problems controlling movements or muscle twitching
- fast heartbeat
- seizures
- loss of coordination

- confusion
- dizziness
- change in blood pressure
- sweating or fever
- nausea, vomiting, or diarrhea
- muscle stiffness or tightness
- high body temperature (hyperthermia)

- New or worsening tics or worsening Tourette’s Syndrome. Tell your healthcare provider if you or your child get any new or worsening tics or worsening Tourette’s syndrome during treatment with ADDERALL XR.

The most common side effects of ADDERALL XR in children ages 6 to 12 include:

- loss of appetite
- trouble sleeping
- stomach (abdominal) pain
- mood swings

- vomiting
- nervousness
- nausea
- fever

The most common side effects of ADDERALL XR in adolescents ages 13 to 17 include:

- loss of appetite
- trouble sleeping
- stomach (abdominal pain)

- weight loss
- nervousness

The most common side effects of ADDERALL XR in adults include:

- dry mouth
- loss of appetite
- trouble sleeping
- headache
- weight loss
- nausea
- anxiety

- agitation
- dizziness
- fast heartbeat
- diarrhea
- weakness
- urinary tract infections (UTIs)

These are not all the possible side effects of ADDERALL XR.

Call your doctor for medical advice about side effects. You may report side effects to FDA at 1-800-FDA-1088.

How should I store ADDERALL XR?

- Store ADDERALL XR at room temperature between 68 to 77°F (20 to 25°C).
- Protect ADDERALL XR from light.
- Store ADDERALL XR in a safe place, like a locked cabinet.
- Dispose of remaining, unused, or expired ADDERALL XR by a medicine take-back program at a U.S. Drug Enforcement Administration (DEA) authorized collection site. If no take-back program or DEA authorized collector is available, mix ADDERALL XR with an undesirable, nontoxic substance such as dirt, cat litter, or used coffee grounds to make it less appealing to children and pets. Place the mixture in a container such as a sealed plastic bag and throw away ADDERALL XR in the household trash. Visit www.fda.gov/drugdisposal for additional information on disposal of unused medicines.

Keep ADDERALL XR and all medicines out of the reach of children.

General information about the safe and effective use of ADDERALL XR.
Medicines are sometimes prescribed for purposes other than those listed in a Medication Guide. Do not use ADDERALL XR for a condition for which it was not prescribed. Do not give ADDERALL XR to other people, even if they have the same condition. It may harm them and it is against the law.

You can ask your healthcare provider or pharmacist for information about ADDERALL XR that is written for healthcare professionals.

What are the ingredients in ADDERALL XR?

Active ingredient: dextroamphetamine sulfate, amphetamine sulfate, dextroamphetamine saccharate, and amphetamine aspartate monohydrate

Inactive ingredients: gelatin capsules, hydroxypropyl methylcellulose, methacrylic acid copolymer, Opadry® beige, sugar spheres, talc, and triethyl citrate. Gelatin capsules contain edible inks, kosher gelatin, and titanium dioxide. The 5 mg, 10 mg, and 15 mg capsules also contain FD&C Blue #2. The 20 mg, 25 mg, and 30 mg capsules also contain red iron oxide and yellow iron oxide

Distributed by:
Takeda Pharmaceuticals America, Inc, Cambridge, MA 02142

ADDERALL XR is a registered trademark of Takeda Pharmaceuticals U.S.A., Inc.
OPADRY is a registered trademark of BPSI Holdings, LLC.
© 2025 Takeda Pharmaceuticals U.S.A., Inc. All rights reserved.

For more information, you may also contact Takeda Pharmaceuticals (the maker of ADDERALL XR) at 1-877-825-3327 or visit the website at http://www.adderallxr.com.

This Medication Guide has been approved by the U.S. Food and Drug Administration.

ADL364 Revised: 09/2025

PRINCIPAL DISPLAY PANEL - 5 mg Capsule Bottle Label

NDC 54092-381-01

ADDERALL XR®
(Mixed Salts of A Single-Entity
Amphetamine Product)

Extended-Release Capsules

5 mg
CII
100 Capsules
Rx only

Takeda

PRINCIPAL DISPLAY PANEL - 10 mg Capsule Bottle Label

NDC 54092-383-01

ADDERALL XR®
(Mixed Salts of A Single-Entity
Amphetamine Product)

Extended-Release Capsules

10 mg
CII
100 Capsules
Rx only

Takeda

PRINCIPAL DISPLAY PANEL - 15 mg Capsule Bottle Label

NDC 54092-385-01

ADDERALL XR®
(Mixed Salts of A Single-Entity
Amphetamine Product)

Extended-Release Capsules

15 mg
CII
100 Capsules
Rx only

Takeda

PRINCIPAL DISPLAY PANEL - 20 mg Capsule Bottle Label

NDC 54092-387-01

ADDERALL XR®
(Mixed Salts of A Single-Entity
Amphetamine Product)

Extended-Release Capsules

20 mg
CII
100 Capsules
Rx only

Takeda

PRINCIPAL DISPLAY PANEL - 25 mg Capsule Bottle Label

NDC 54092-389-01

ADDERALL XR®
(Mixed Salts of A Single-Entity
Amphetamine Product)

Extended-Release Capsules

25 mg
CII
100 Capsules
Rx only

Takeda

PRINCIPAL DISPLAY PANEL - 30 mg Capsule Bottle Label

NDC 54092-391-01

ADDERALL XR®
(Mixed Salts of A Single-Entity
Amphetamine Product)

Extended-Release Capsules

30 mg
CII
100 Capsules
Rx only

Takeda